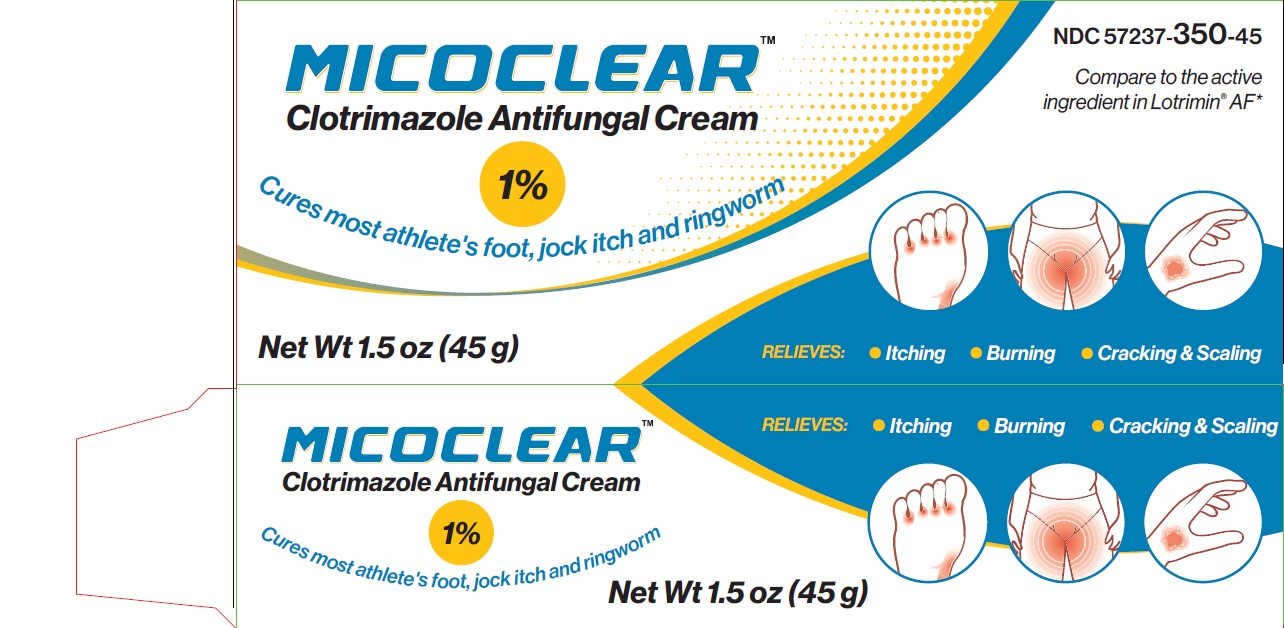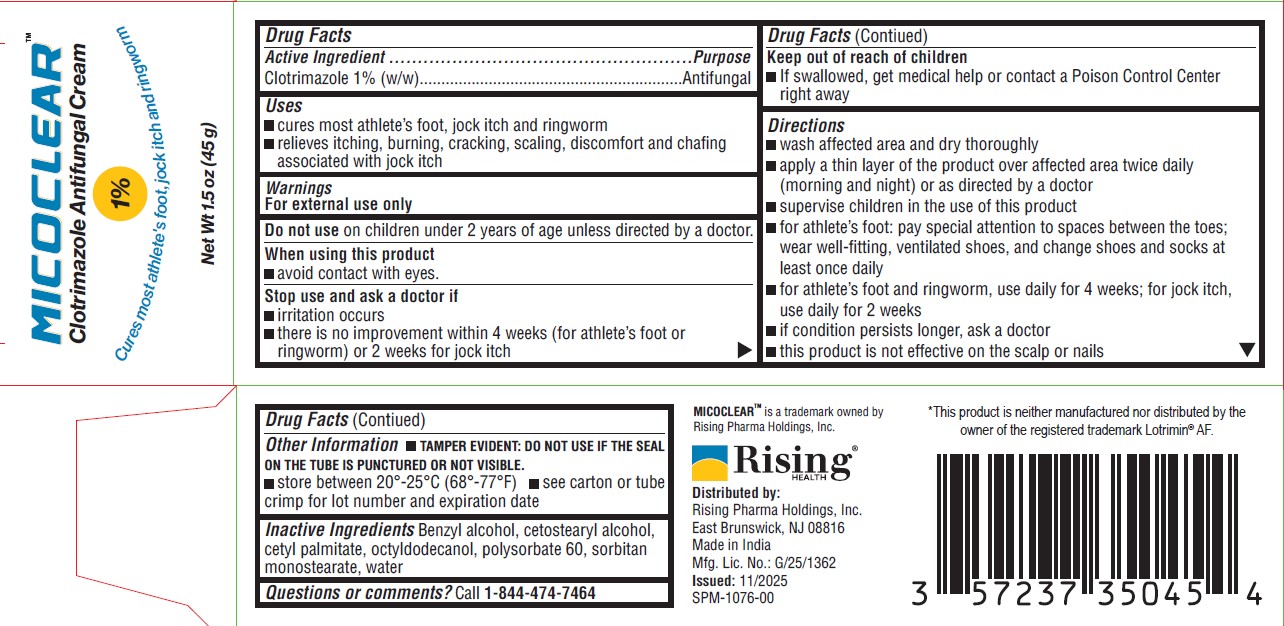 DRUG LABEL: MICOCLEAR
NDC: 57237-350 | Form: CREAM
Manufacturer: Rising Pharma Holdings, Inc.
Category: otc | Type: HUMAN OTC DRUG LABEL
Date: 20251106

ACTIVE INGREDIENTS: CLOTRIMAZOLE 10 mg/1 g
INACTIVE INGREDIENTS: BENZYL ALCOHOL; CETOSTEARYL ALCOHOL; CETYL PALMITATE; OCTYLDODECANOL; POLYSORBATE 60; WATER; SORBITAN MONOSTEARATE

MICOCLEAR™
Clotrimazole Antifungal Cream 1%
Cures most athlete's foot, jock itch and ringworm

Drug Facts

Active Ingredient

Clotrimazole 1% (w/w)

Purpose

Antifungal

Uses

- cures most athlete's foot, jock itch and ringworm
- relieves itching, burning, cracking, scaling, discomfort and chafing associated with jock itch

Warnings

For external use only

Do not use on children under 2 years of age unless directed by a doctor.

When using this product

- avoid contact with eyes.

Stop use and ask a doctor if

- irritation occurs
- there is no improvement within 4 weeks (for athlete's foot or ringworm) or 2 weeks for jock itch

Keep out of reach of children

- If swallowed, get medical help or contact a Poison Control Center right away

Directions

- wash affected area and dry thoroughly
- apply a thin layer of the product over affected area twice daily (morning and night) or as directed by a doctor
- supervise children in the use of this product
- for athlete's foot: pay special attention to spaces between the toes; wear well-fitting, ventilated shoes, and change shoes and socks at least once daily
- for athlete's foot and ringworm, use daily for 4 weeks; for jock itch, use daily for 2 weeks
- if condition persists longer, ask a doctor
- this product is not effective on the scalp or nails

Other Information

- TAMPER EVIDENT: DO NOT USE IF THE SEAL ON THE TUBE IS PUNCTURED OR NOT VISIBLE.
- store between 20°-25°C (68°-77°F)
- see carton or tube crimp for lot number and expiration date

Inactive Ingredients

Benzyl alcohol, cetostearyl alcohol, cetyl palmitate, octyldodecanol, polysorbate 60, sorbitan monostearate, water

Questions or comments?

Call 1-844-474-7464

MICOCLEARTM is a trademark owned by Rising Pharma Holdings, Inc.

Distributed by:

Rising Pharma Holdings, Inc.
East Brunswick, NJ 08816
Made in India
Mfg.Lic.No.: G/25/1362

PRINCIPAL DISPLAY PANEL -45g carton

MICOCLEARTM

Clotrimazole Antifungal Cream 1%

Cures most athlete's foot, jock itch and ringworm

Net Wt 1.5 oz (45 g)